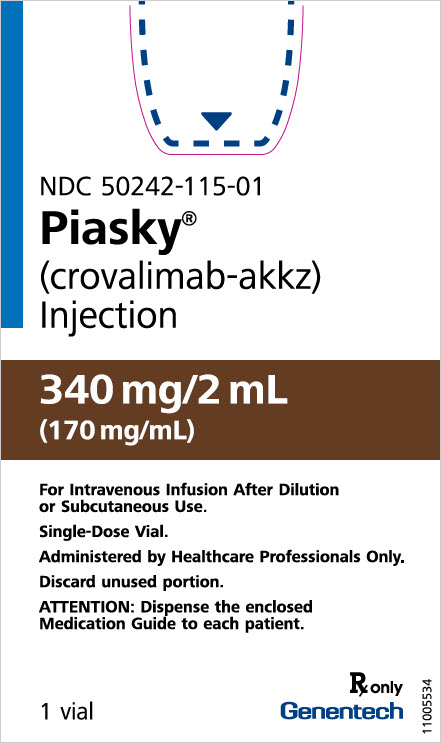 DRUG LABEL: Piasky
NDC: 50242-115 | Form: INJECTION, SOLUTION
Manufacturer: Genentech, Inc.
Category: prescription | Type: HUMAN PRESCRIPTION DRUG LABEL
Date: 20251111

ACTIVE INGREDIENTS: CROVALIMAB 340 mg/2 mL
INACTIVE INGREDIENTS: HISTIDINE; ASPARTIC ACID; ARGININE HYDROCHLORIDE; POLOXAMER 188; WATER

HIGHLIGHTS OF PRESCRIBING INFORMATION

These highlights do not include all the information needed to use PIASKY safely and effectively. See full prescribing information for PIASKY.
PIASKY (crovalimab-akkz) injection, for intravenous or subcutaneous use
Initial U.S. Approval: 2024

WARNING: SERIOUS MENINGOCOCCAL INFECTIONS

See full prescribing information for complete boxed warning.

PIASKY increases the risk of serious and life-threatening infections caused by Neisseria meningitidis.

- Complete or update meningococcal vaccination at least 2 weeks prior to the first dose of PIASKY, unless the risks of delaying PIASKY outweigh the risks of developing a serious infection. Comply with the most current Advisory Committee on Immunization Practices (ACIP) recommendations for meningococcal vaccination in patients receiving a complement inhibitor (5.1).
- Patients receiving PIASKY are at increased risk for invasive disease caused by N. meningitidis, even if they develop antibodies following vaccination. Monitor patients for early signs of meningococcal infections and evaluate immediately if infection is suspected (5.1).

PIASKY is available only through a restricted program called the PIASKY REMS (5.2)

1 INDICATIONS AND USAGE

PIASKY is a complement C5 inhibitor indicated for the treatment of adult and pediatric patients 13 years and older with paroxysmal nocturnal hemoglobinuria (PNH) and body weight of at least 40 kg (1)

2 DOSAGE AND ADMINISTRATION

See Full Prescribing Information for instructions on preparation, dosage, and administration. (2.2, 2.3, 2.4, 2.5)

Start with one loading dose administered by intravenous infusion, followed by 4 additional loading doses administered by subcutaneous injection. Then administer a maintenance dose every 4 weeks by subcutaneous injection.

For patients switching from another complement inhibitor, the first loading dose of PIASKY should be administered no sooner than the time of the next scheduled complement inhibitor administration. See Full Prescribing Information for considerations when switching from another C5 inhibitor.

Administer doses based on the patient's actual body weight (2.2)

3 DOSAGE FORMS AND STRENGTHS

Injection: 340 mg/2 mL (170 mg/mL) in a single-dose vial (3)

4 CONTRAINDICATIONS

- Initiation during unresolved serious Neisseria meningitidis infection (4)
- Serious hypersensitivity to crovalimab or any of the excipients (4)

5 WARNINGS AND PRECAUTIONS

- Type III hypersensitivity reactions: Monitor patients switching from another C5 inhibitor to PIASKY or from PIASKY to another C5 inhibitor as they are at risk of Type III hypersensitivity reactions related to the formation of drug-target-drug complexes (5.3)
- Other Infections: PIASKY can increase susceptibility to serious infections especially those caused by encapsulated bacteria. (5.4)
- Infusion- and Injection-Related Reactions: Monitor for these reactions and initiate medical management as needed (5.5)

6 ADVERSE REACTIONS

The most common adverse drug reactions (incidence ≥10%) were infusion-related reaction, respiratory tract infection, viral infection, and Type III hypersensitivity reactions. (6.1)

To report SUSPECTED ADVERSE REACTIONS, contact Genentech at 1-888-835-2555 or FDA at 1-800-FDA-1088 or www.fda.gov/medwatch.

8. USE IN SPECIFIC POPULATIONS

Lactation: Breastfeeding not recommended (8.2)

FULL PRESCRIBING INFORMATION

WARNING: SERIOUS MENINGOCOCCAL INFECTIONS

PIASKY, a complement inhibitor, increases the risk of serious infections caused by Neisseria meningitidis [see Warnings and Precautions (5.1)]. Life-threatening and fatal meningococcal infections have occurred in patients treated with complement inhibitors. These infections may become rapidly life-threatening or fatal if not recognized and treated early.

- Complete or update vaccination for meningococcal bacteria (for serogroups A, C, W, Y, and B) at least 2 weeks prior to the first dose of PIASKY, unless the risks of delaying therapy with PIASKY outweigh the risk of developing a serious infection. Comply with the most current Advisory Committee on Immunization Practices (ACIP) recommendations for meningococcal vaccination in patients receiving a complement inhibitor. See Warnings and Precautions (5.1) for additional guidance on the management of the risk of serious infections caused by meningococcal bacteria.
- Patients receiving PIASKY are at increased risk for invasive disease caused by N. meningitidis, even if they develop antibodies following vaccination. Monitor patients for early signs of serious meningococcal infections and evaluate immediately if infection is suspected.

Because of the risk of serious meningococcal infections, PIASKY is available only through a restricted program under a Risk Evaluation and Mitigation Strategy (REMS) called PIASKY REMS [see Warnings and Precautions (5.2)].

1 INDICATIONS AND USAGE

PIASKY is indicated for the treatment of adult and pediatric patients 13 years and older with paroxysmal nocturnal hemoglobinuria (PNH) and body weight of at least 40 kg.

2 DOSAGE AND ADMINISTRATION

2.1 Recommended Vaccination and Prophylaxis for Meningococcal Infection

Vaccinate patients for meningococcal infection (serogroups A, C, W, Y and B) according to current ACIP recommendations at least 2 weeks prior to initiation of PIASKY [see Warnings and Precautions (5.1)].

If urgent PIASKY therapy is indicated in a patient who is not up to date with meningococcal vaccines according to ACIP recommendations, provide the patient with antibacterial drug prophylaxis and administer these vaccines as soon as possible.

Healthcare providers who prescribe PIASKY must enroll in the PIASKY REMS [see Warnings and Precautions (5.2)].

2.2 Recommended Dosage Regimen

The recommended dosage regimen consists of one loading dose administered by intravenous (IV) infusion (on Day 1), followed by four additional weekly loading doses administered by subcutaneous (SUBQ) injection (on Days 2, 8, 15, and 22). The maintenance dose starts on Day 29 and is then administered every 4 weeks by subcutaneous injection. Administer doses based on the patient's actual body weight, as shown in Table 1.

Table 1 PIASKY Dosage Regimen Based on Body Weight
Body Weight | ≥ 40 kg to < 100 kg | ≥ 100 kg
Loading Dose Day 1 Day 2, 8, 15, 22 | 1,000 mg (IV) 340 mg (SUBQ) | 1,500 mg (IV) 340 mg (SUBQ)
Maintenance Dose Day 29 and Q4W [Q4W=every 4 weeks] thereafter | 680 mg (SUBQ) | 1,020 mg (SUBQ)
IV = intravenous, SUBQ = subcutaneous

The dosing schedule is allowed to occasionally vary within 2 days of the scheduled administration day (except at Day 1 and Day 2). If this occurs, the subsequent dose should be administered according to the regular schedule.

Modification of the maintenance dose is required if the patient's body weight changes to become consistently greater than or lower than 100 kg during the course of therapy.

2.3 Recommended Timing for Switching to PIASKY from Another C5 Inhibitor

Healthcare providers should consider the benefits of the timing of switching C5 inhibitors vs. the risks of Type III hypersensitivity reactions [see Warnings and Precautions (5.3)]. For patients switching from another C5 inhibitor (e.g., eculizumab or ravulizumab), the first intravenous loading dose of PIASKY should be administered no sooner than the time of the next scheduled complement inhibitor administration. The administration of the additional subcutaneous loading doses and maintenance doses of PIASKY should follow as per the schedule shown in Table 1.

2.4 Delayed or Missed Dose

If an entire planned dose or part of a planned dose of PIASKY is missed, administer the missed dose or remainder of the missed dose as soon as possible before the day of the next scheduled dose. Then administer the next dose on the regularly scheduled dosing day. Do not administer two doses or more than the prescribed dose on the same day to make up for a missed dose.

2.5 Preparation and Administration

Each vial of PIASKY is for one-time use in only one patient.

PIASKY is administered as an intravenous infusion (first dose) and as a subcutaneous injection (subsequent doses). Only healthcare providers should administer PIASKY.

Parenteral drug products should be inspected visually for particulate matter and discoloration prior to administration, whenever solution and container permit. PIASKY is clear to opalescent, and an almost colorless to brownish-yellow solution. PIASKY should be discarded if the medicine looks cloudy, discolored, or has particles in it.

Preparation of Intravenous Infusion

- Use aseptic technique to prepare PIASKY for intravenous administration. PIASKY must be diluted and administered as an intravenous infusion over 60 minutes ± 10 minutes (1,000 mg) or 90 minutes ± 10 minutes (1,500 mg).
- PIASKY solution must be diluted in 0.9% Sodium Chloride Injection prior to administration. A 0.2 micron in-line filter must be used with the infusion set during administration. A dedicated infusion line must be used during intravenous administration.
- Only dilute PIASKY in 0.9% Sodium Chloride Injection.

Dilution of Intravenous Infusion

- Withdraw the required volume of PIASKY from the vial (see Table 2) using a sterile syringe and dilute into the infusion bag. Use multiple vials to meet the required volume of PIASKY to be added to the infusion bag. Discard any unused portion left in the vial.

Dilution of PIASKY in infusion bags containing 0.9% Sodium Chloride Injection must be in the range of 4-15 mg/mL (final concentration after dilution) (see Table 2).

Intravenous infusion bags of a volume of 100 mL or 250 mL can be used.

Table 2 Dose Example Volume Determination
Dose (mg) | Volume of Piasky (mL) | Size of 0.9% Sodium Chloride Injection Bag (mL) | Concentration in Bag (mg/mL)
1,000 | 5.9 | 250 | 4
1,500 | 8.8 | 250 | 6
1,000 | 5.9 | 100 | 10
1,500 | 8.8 | 100 | 15

- Gently mix the infusion bag by slowly inverting the bag. Do not shake.
- Inspect the infusion bag for particles and discard if present.
- Flushing of infusion line is required to ensure complete administration of the entire dose.

Storage of Diluted Solution for Infusion

The diluted solution for intravenous infusion should be used immediately because PIASKY does not contain any antimicrobial preservative. If immediate use is not possible, see Table 3 for detailed storage conditions of the prepared solution for infusion, which depends on the type of infusion bags used.

Table 3 Storage Conditions for the Prepared Solution for Infusion
Infusion bags | Storage conditions
PO/PE/PP | Refrigerate at 2°C to 8°C (36°F to 46°F) for up to 64 hours protected from light, and store at room temperature up to 30°C (86°F) for up to 6 hours including infusion time under ambient light conditions. Protect from direct sunlight.
PVC | Refrigerate at 2°C to 8°C (36°F to 46°F) for up to 12 hours protected from light, and store at room temperature up to 30°C (86°F) for up to 6 hours including infusion time under ambient light conditions. Protect from direct sunlight.
polyolefins (PO), polyethylene (PE), polypropylene (PP), polyvinyl chloride (PVC)

No incompatibilities have been observed between PIASKY and intravenous infusion bags with product-contacting materials made of polyvinyl chloride, or polyolefins such as polyethylene and polypropylene. In addition, no incompatibilities have been observed with infusion sets or infusion aids with product-contacting materials made of polyvinyl chloride, polyethylene, polyurethane, polybutadiene, acrylonitrile butadiene styrene, polycarbonate, or polytetrafluorethylene.

The infusion of PIASKY may be slowed or interrupted if the patient develops an infusion-related reaction. The infusion should be discontinued immediately if the patient experiences a serious hypersensitivity reaction [see Warnings and Precautions (5.5)].

Preparation of the Subcutaneous Injection

For subcutaneous injection, PIASKY must be used undiluted.

- Remove the vial cap and clean the vial rubber stopper.
- Attach the transfer needle on the syringe.
- Withdraw all the medicine from the vial.
  - Remove air bubbles if any.
- Remove the transfer needle from the vial.
  - Recap the transfer needle using a one-handed scoop technique.
  - Detach the transfer needle.
- Attach the injection needle on the syringe.
- Clean the injection site with an alcohol pad and let air dry.
- Inject the medicine subcutaneously.

If the dose requires multiple injections, perform a new injection using a new PIASKY vial.

A syringe, a transfer needle and an injection needle are needed to withdraw PIASKY solution from the vial and inject it subcutaneously.

  - A 2 mL or 3 mL syringe fulfilling the following criteria are recommended: Transparent polypropylene or polycarbonate syringe with Luer-Lock tip (if not available, a syringe with Luer Slip tip can be used), sterile, single-use, latex-free and non-pyrogenic, and commercially available in the US.
  - A transfer needle without a filter fulfilling the following criteria may be used: Stainless steel, sterile, preferably gauge 18 G with single bevel at approximately 45 degrees to reduce risk of needle stick injury (or gauge 21 G standard needle as an alternative), single-use, latex-free and non-pyrogenic, and commercially available in the US.
  - An injection needle fulfilling the following criteria may be used: Hypodermic needle, stainless steel, sterile, gauge 25 G, 26 G or 27 G, length 3/8'' to 1/2'', single-use, latex-free and non-pyrogenic, preferably including safety needle shield, and commercially available in the US.

- Each injection is a volume of 2 mL PIASKY, corresponding to 340 mg. A 2 mL-size or 3 mL-size syringe should be used for each injection. A dose of 680 mg is achieved by performing two consecutive subcutaneous injections of 340 mg. A dose of 1020 mg is achieved by performing three consecutive subcutaneous injections of 340 mg.
- Inject PIASKY subcutaneously in the abdomen region and rotate abdominal injection sites with every injection. Consecutive injections must be at least 2 inches apart. No data are available on injection at other sites of the body. Injections should never be given into moles, scars, or areas where the skin is tender, bruised, red, hard, or not intact.

Storage of Solution for Injection

Once transferred from the vial to the syringe, PIASKY should be injected immediately because PIASKY does not contain any antimicrobial-preservative. If immediate use is not possible, the capped syringe can be refrigerated at 2°C to 8°C (36°F to 46°F) for up to 64 hours protected from light and stored at room temperature up to 30°C (86°F) for up to 5 hours under ambient light conditions.

Protect from direct sunlight.

3 DOSAGE FORMS AND STRENGTHS

Injection: 340 mg/2 mL (170 mg/mL) as a clear to opalescent and almost colorless to brownish-yellow solution in a single-dose vial.

4 CONTRAINDICATIONS

PIASKY is contraindicated:

- For initiation in patients with an unresolved serious Neisseria meningitidis infection [see Warnings and Precautions (5.1)].
- In patients with a known serious hypersensitivity reaction to crovalimab or any of the excipients [see Warnings and Precautions (5.5)].

5 WARNINGS AND PRECAUTIONS

5.1 Serious Meningococcal Infection

PIASKY, a complement inhibitor, increases a patient's susceptibility to serious, life-threatening, or fatal infections caused by meningococcal bacteria (meningococcemia and/or meningitis) in any serogroup, including non-groupable strains. Life-threatening and fatal meningococcal infections have occurred in both vaccinated and unvaccinated patients treated with complement inhibitors. The initiation of PIASKY is contraindicated in patients with a serious unresolved Neisseria meningitidis infection.

Complete or update meningococcal vaccination (for serogroups A, C, W, Y, and B) at least 2 weeks prior to administration of the first dose of PIASKY, according to the current Advisory Committee on Immunization Practices (ACIP) recommendations for patients receiving a complement inhibitor. Revaccinate patients in accordance with ACIP recommendations considering the duration of PIASKY therapy.

Note that ACIP recommends an administration schedule in patients receiving complement inhibitors that differs from the administration schedule in the vaccine prescribing information.

If urgent PIASKY therapy is indicated in a patient who is not up to date with meningococcal vaccines according to ACIP recommendations, provide the patient with antibacterial drug prophylaxis and administer meningococcal vaccines as soon as possible. Various durations and regimens of antibacterial drug prophylaxis have been considered, but the optimal durations and drug regimens for prophylaxis and their efficacy have not been studied in unvaccinated or vaccinated patients receiving complement inhibitors, including PIASKY. The benefits and risks of treatment with PIASKY, as well as the benefits and risks of antibacterial drug prophylaxis in unvaccinated or vaccinated patients, must be considered against the known risks for serious infections caused by N. meningitidis.

Vaccination does not eliminate the risk of meningococcal infections, despite development of antibodies following vaccination.

Closely monitor patients for early signs and symptoms of meningococcal infection and evaluate patients immediately if infection is suspected. Inform patients of these signs and symptoms and instruct patients to seek immediate medical care if these signs and symptoms occur. Promptly treat known infections. Meningococcal infection may become rapidly life-threatening or fatal if not recognized and treated early. Consider interruption of PIASKY in patients who are undergoing treatment for serious meningococcal infection.

PIASKY is available only through a restricted program under a REMS [see Warnings and Precautions (5.2)].

5.2 PIASKY REMS

PIASKY is available only through a restricted program under a REMS called PIASKY REMS, because of the risk of serious meningococcal infections [see Warnings and Precautions (5.1)].

Notable requirements of the PIASKY REMS include the following:

- Prescribers must enroll in the REMS.
- Prescribers must counsel patients about the risk of serious meningococcal infection.
- Prescribers must provide the patients with the REMS educational materials.
- Prescribers must assess patient vaccination status for meningococcal vaccines (against serogroups A, C, W, Y, and B) and vaccinate if needed according to current ACIP recommendations two weeks prior to the first dose of PIASKY.
- Prescribers must provide a prescription for antibacterial drug prophylaxis if treatment must be started urgently, and the patient is not up to date with both meningococcal vaccines according to current ACIP recommendations at least two weeks prior to the first dose of PIASKY.
- Healthcare settings and pharmacies that dispense PIASKY must be certified in the REMS and must verify prescribers are certified.
- Patients must receive counseling from the prescriber about the need to receive meningococcal vaccines per ACIP recommendations, the need to take antibiotics as directed by the prescriber, and the signs and symptoms of meningococcal infection.
- Patients must be instructed to carry the Patient Safety Card with them at all times during and for 11 months following treatment with PIASKY.

Further information is available at www.PIASKYREMS.com or 1-866-4My-Skyy (469-7599).

5.3 Type III Hypersensitivity Reactions Related to Drug-Target-Drug Complexes

Patients who are switching from another C5 inhibitor (e.g., eculizumab or ravulizumab) to PIASKY or from PIASKY to another C5 inhibitor are at risk of serious Type III hypersensitivity reactions related to the formation of drug-target-drug-complexes (DTDCs), because PIASKY and these other C5 inhibitors bind different epitopes of C5 [see Drug Interactions (7)].

In clinical trials, Type III hypersensitivity reactions were reported in 39 of 201 patients (19%) who switched from eculizumab or ravulizumab to PIASKY. Four of these patients (10%) had not fully recovered from symptoms of Type III hypersensitivity reactions at the time of their last follow up visit. In addition, Type III hypersensitivity reactions were reported in 2 of 8 patients (25%) who switched from PIASKY to eculizumab or ravulizumab, including one patient who developed Grade 3 axonal neuropathy [see Adverse Reactions (6)].

Symptoms of Type III hypersensitivity reactions that occurred in more than 2 patients were arthralgia, rash, pyrexia, myalgia, headache, fatigue, petechiae and abdominal pain. Among patients who experienced Type III hypersensitivity reactions, 8 (21%) had events that were considered serious due to hospitalization. Symptoms of serious Type III hypersensitivity reactions included pyrexia and arthralgia. Type III hypersensitivity reactions can also cause renal abnormalities.

Healthcare providers should consider the benefits of the timing of switching C5 inhibitors vs. the risks of Type III hypersensitivity reactions. Patients are expected to no longer be at risk of Type III hypersensitivity reactions if the prior C5 inhibitor has been cleared from the body prior to starting PIASKY or if PIASKY has been cleared from the body prior to starting another C5 inhibitor. Therefore, initiating PIASKY sooner than 5.5 half-lives from the last dose of a C5 inhibitor (e.g., eculizumab or ravulizumab) or initiating a C5 inhibitor (e.g., eculizumab or ravulizumab) sooner than 5.5 half-lives from the last dose of PIASKY increases the risk of Type III hypersensitivity reactions.

Based on time-to-onset of Type III hypersensitivity reactions observed in clinical trials, patients should be monitored for the first 30 days of the new therapy for the occurrence of symptoms of Type III hypersensitivity reactions. For mild or moderate Type III hypersensitivity reactions, administer symptomatic treatment, such as topical corticosteroids, antihistamines, antipyretics, and/or analgesics. For severe reactions, initiate and taper oral or systemic corticosteroid therapy as clinically indicated.

5.4 Other Infections

Due to its mechanism of action, PIASKY may increase susceptibility to infections, especially with encapsulated bacteria, such as infections with Neisseria spp. but also Streptococcus pneumoniae, Haemophilus influenzae, and to a lesser extent, Neisseria gonorrhoeae. Children treated with PIASKY may be at increased risk of developing serious infections due to Streptococcus pneumoniae and Haemophilus influenzae type b (Hib). Vaccinate patients against Streptococcus pneumoniae and Haemophilus influenzae type b (Hib) infections according to ACIP recommendations.

If PIASKY is administered to patients with active systemic infections, monitor closely for signs and symptoms of worsening infection. If the patient's infection worsens, consider whether to discontinue PIASKY.

5.5 Infusion- and Injection-Related Reactions

Administration of PIASKY may cause infusion-related reactions or systemic injection-related reactions, depending on the route of administration [see Adverse Reactions (6)]. These may include hypersensitivity reactions (including anaphylaxis) but also a range of other symptoms such as injection site pain, erythema, headache or myalgia. One patient experienced a serious infusion-related reaction that resolved 4 days after interruption of infusion with PIASKY. Instruct patients/caregivers to seek immediate medical attention if the patient develops symptoms of a serious hypersensitivity reaction and to report this reaction to their healthcare provider.

If a serious hypersensitivity reaction (including anaphylaxis) occurs, discontinue PIASKY treatment immediately, institute appropriate treatment, per standard of care, and monitor until signs and symptoms are resolved. PIASKY is contraindicated in patients with a known serious hypersensitivity reaction to crovalimab or any of the excipients.

5.6 Monitoring PNH Manifestations after Discontinuation of PIASKY

In case of PIASKY discontinuation, patients who do not switch to another treatment for PNH, must be closely monitored for at least 20 weeks for signs and symptoms of serious hemolysis, identified by elevated lactate dehydrogenase (LDH) levels, along with a sudden decrease in hemoglobin, or re-appearance of symptoms such as fatigue, hemoglobinuria, abdominal pain, dyspnea, major adverse vascular events (including thrombosis), dysphagia, erectile dysfunction or renal impairment.

If signs and symptoms of hemolysis occur after discontinuation of PIASKY, consider restarting treatment with PIASKY, if appropriate, or initiating another treatment for PNH.

6 ADVERSE REACTIONS

The following clinically significant adverse reactions are discussed in greater detail in other sections of the label:

- Serious Meningococcal Infection [see Warnings and Precautions (5.1)]
- Type III Hypersensitivity Reactions Related to Drug-Target-Drug Complexes [see Warnings and Precautions (5.3)]
- Other Infections [see Warnings and Precautions (5.4)]
- Infusion- and Injection-Related Reactions [see Warnings and Precautions (5.5)]

6.1 Clinical Trial Experience

Because clinical trials are conducted under widely varying conditions, adverse reaction rates observed in the clinical trials of a drug cannot be directly compared to rates in the clinical trials of another drug and may not reflect the rates observed in practice.

Patients Who are Complement Inhibitor-Naïve

The data described below reflect exposure of 204 patients with PNH who were complement inhibitor-naïve and who were randomized in COMMODORE 2 to receive PIASKY (n = 135) or eculizumab (n = 69) at the recommended dosing regimen for 24 weeks [see Clinical Studies (14)].

Serious adverse reactions occurred in 6% of patients receiving PIASKY in the COMMODORE 2 study, including epistaxis and pneumonia, which occurred in 2 patients each, and infusion related reaction, pyelonephritis, COVID-19, and hypovolemic shock which were reported in 1 patient each.

Table 4 lists adverse reactions that occurred at a rate of 5% or more among patients randomized to PIASKY treatment for 24 weeks in the COMMODORE 2 study. The most common adverse reactions (≥10%) in patients treated with PIASKY were infusion related reaction, respiratory tract infection, and viral infection.

Table 4 Adverse Reactions Reported In 5% or More of Complement-Inhibitor Naïve Patients with PNH Randomized to PIASKY in COMMODORE 2
Adverse reactions | PIASKY (N = 135) % | ECULIZUMAB (N = 69) %
Infusion-related reaction | 16 | 13
Respiratory tract infection [Grouped terms. Diarrhea includes diarrhea and diarrhea infectious. Headache includes headache and migraine. Injection-related reaction includes injection related reaction and injection site reaction. Respiratory tract infection includes nasopharyngitis, pharyngitis, rhinitis, rhinitis allergic, upper respiratory tract infection and pneumonia. Viral infection includes viral infection, COVID-19, influenza, herpes virus infection and oral herpes.] | 13 | 20
Viral infection | 11 | 7
Hyperuricemia | 8 | 9
Headache | 8 | 6
Diarrhea | 7 | 1
Injection-related reaction [Injection-related reactions are only expected to occur in the PIASKY arm as eculizumab is not given by subcutaneous injection] | 6 | 0

Patients Previously Treated with a Complement C5 Inhibitor

The data described below reflect exposure of 86 patients with PNH who received PIASKY (n=44) or eculizumab (n=42) at the recommended dosing regimen for 24 weeks in COMMODORE 1, an open-label, active-controlled, multicenter study conducted in patients switching from eculizumab. The median age was 47 years (range: 21 to 85); 52% were female, and race included White (73%), Asian (19%), unknown (5%), and Black/African-American (3%). The population ethnicities were 17% Hispanic or Latino and 76% not Hispanic or Latino.

Serious adverse reactions in COMMODORE 1 were reported in 3 patients (7%) with PNH receiving PIASKY. Serious adverse reactions included pneumonia, nasopharyngitis, and urinary tract infection, which occurred in 1 patient each.

Table 5 lists adverse reactions that occurred at a rate of 5% or more among patients randomized to PIASKY treatment for 24 weeks in the COMMODORE 1 study. The most common adverse reactions (≥10%) in patients treated with PIASKY were viral infections, respiratory tract infection, Type III hypersensitivity reaction, infusion-related reaction, peripheral edema, and headache.

Table 5 Adverse Reactions Reported In 5% or More of Complement-Inhibitor Treated Patients with PNH Randomized to PIASKY in COMMODORE 1
Adverse reactions | PIASKY (N = 44) % | ECULIZUMAB (N = 42) %
Viral infection [Grouped terms Fatigue includes fatigue, malaise and asthenia. Injection-related reaction includes injection related reaction and injection site reaction. Rash includes rash and skin exfoliation. Peripheral edema includes edema peripheral and peripheral swelling. Respiratory tract infection includes respiratory tract infection, nasopharyngitis, pneumonia and upper respiratory tract infection. Viral infection includes viral infection, influenza, COVID-19, and respiratory syncytial virus infection] | 23 | 21
Respiratory tract infection | 18 | 5
Type III hypersensitivity reaction [Type III immune complex mediated reaction is only expected to occur in the PIASKY arm as patients in the eculizumab arm did not change C5 inhibitor treatment] | 16 | 0
Infusion-related reaction [Infusion-related reactions are not expected to occur in the eculizumab arm as these patients tolerated eculizumab prior to study initiation] | 14 | 0
Peripheral edema | 11 | 2
Headache | 11 | 2
Injection-related reaction [Injection-related reactions are only expected to occur in the PIASKY arm as eculizumab is not given by subcutaneous injection] | 9 | 0
Fatigue | 9 | 12
Rash | 9 | 0
Diarrhea | 7 | 2
Nausea | 7 | 5
Arthralgia | 7 | 0

Type III Hypersensitivity Reactions Related to Drug-Target-Drug Complexes [see Warnings and Precautions (5.3), and Drug Interactions (7)].

Across the COMMODORE 1 and 2 studies, 39 out of 201 (19.4%) patients who switched from eculizumab or ravulizumab to PIASKY experienced a Type III hypersensitivity reaction (reported as Type III immune complex mediated reaction). A total of 6 patients had switched two times and of the 6 patients, 2 patients experienced a second episode of Type III hypersensitivity reaction after discontinuing PIASKY and switching to ravulizumab. One of these patients developed Grade 3 axonal neuropathy and a Type III hypersensitivity reaction could not be excluded and the other developed Grade 2 arthralgia and myalgia. These two events remained unresolved at the last follow up visit of the clinical studies (the duration of the events until last follow-up was 313 days for the event of Grade 3 axonal neuropathy and 142 days for the event of Grade 2 arthralgia and myalgia, respectively). Two additional patients who experienced Grade 3 rash and Grade 3 arthralgia, respectively, had unresolved Type III hypersensitivity reaction at the last follow-up visit.

The median time to onset of Type III hypersensitivity reaction in patients who switched treatment from eculizumab or ravulizumab to PIASKY was 1.6 weeks (range: 0.7 – 4.4 weeks) and the median duration of Type III hypersensitivity reactions was 1.9 weeks (range 0.4 – 34.1 weeks). The majority of events were Grade 1-2. Grade 3 Type III hypersensitivity reaction occurred in 8% of patients who switched from eculizumab or ravulizumab to PIASKY. Out of 42 Type III hypersensitivity reactions, 37 (88%) resolved, including 1 (2.4%) that resolved with PIASKY discontinuation, 2 (4.8%) that resolved with PIASKY interruption and 34 (81%) that resolved without discontinuation, interruption, or dose change in PIASKY therapy.

Axonal Neuropathy

In COMMODORE 1 and 2, Grade 3 distal axonal demyelinating polyneuropathy and Grade 3 axonal neuropathy were reported, each in 1 patient who switched from another C5 inhibitor to PIASKY or from PIASKY to another C5 inhibitor. The Grade 3 distal axonal demyelinating polyneuropathy occurred 11 weeks after a patient switched from eculizumab to PIASKY (with first dose of PIASKY received 12 days after the last dose of eculizumab treatment) and was preceded by a bacterial respiratory tract infection. The Grade 3 axonal neuropathy occurred in a patient who had switched to ravulizumab treatment after 6 weeks of treatment with PIASKY, and previously received ravulizumab treatment prior to switching to treatment with PIASKY [see Warnings and Precautions (5.3)]. Events associated with the axonal neuropathy included COVID-19, sepsis and administration of a fluoroquinolone. In both cases of axonal neuropathy, a Type III hypersensitivity reaction as a cause of, or contributor to, the axonal neuropathy could not be excluded. Both cases of axonal neuropathy remained unresolved at the last follow up visit of the clinical studies.

Pediatric Population with PNH Treated with PIASKY

Twelve pediatric patients with PNH (9 treatment-naïve patients and 3 patients who switched from another C5 inhibitor) were treated with PIASKY in COMMODORE 1 (n=2), COMMODORE 2 (n=7), and in a single-arm trial [(COMMODORE 3 (n=3)]. The safety profile of PIASKY appeared comparable between adult and pediatric patients, but conclusions are limited by the small number of pediatric patients.

7. DRUG INTERACTIONS

PIASKY binds different epitopes on C5 compared to eculizumab and ravulizumab, which can lead to the formation of DTDCs when patients switch between PIASKY and either eculizumab or ravulizumab. These DTDCs comprise one or more units of C5 bound to both PIASKY and to eculizumab or ravulizumab. These DTDCs are expected to be cleared within approximately 8 weeks (in the case of eculizumab) or longer (in the case of ravulizumab) and can result in Type III hypersensitivity reactions [see Warnings and Precautions (5.3), Adverse Reactions (6.1) and Clinical Pharmacology (12.3)].

8. USE IN SPECIFIC POPULATIONS

8.1 Pregnancy

Risk Summary

Available data on PIASKY use in pregnant women are insufficient to evaluate for a drug associated risk of major birth defects, miscarriage, or other adverse maternal or fetal outcomes. Human IgG antibody is known to cross the placenta and its transport increases as pregnancy progresses and peaks during the third trimester; therefore, PIASKY may be transmitted from the mother to the developing fetus. There are risks to the mother and fetus associated with untreated PNH in pregnancy (see Clinical Considerations). In an enhanced pre- and postnatal development study, no adverse developmental outcomes were observed when monkeys were exposed to crovalimab-akkz during the period of organogenesis through parturition at doses that produced maternal exposures 14-times the exposures at the maximum recommended human dose (MRHD), (see Data).

The background risk of major birth defects and miscarriage for the indicated population is unknown. All pregnancies have a background risk of birth defect, loss, or other adverse outcomes. In the U.S. general population, the estimated background risks of major birth defects and miscarriage in clinically recognized pregnancies are 2-4% and 15-20%, respectively.

Clinical Considerations

Disease-associated maternal and/or fetal/neonatal risk

PNH in pregnancy is associated with adverse maternal outcomes, including worsening cytopenias, thrombosis, infections, bleeding, miscarriages, and increased maternal mortality, and adverse fetal outcomes, including fetal death and premature delivery.

Data

Animal data

In an enhanced pre- and post-natal development study, pregnant cynomolgus monkeys were given an intravenous loading dose of crovalimab-akkz 100 mg/kg on gestation day (GD) 20 followed by weekly subcutaneous injections of up to 100 mg/kg up to parturition. The dams and infants were then observed untreated for 6 months. There were no adverse effects of crovalimab-akkz on pregnancy or on the viability, growth, and development of the infants up to 100 mg/kg at exposures 14-times the human exposure at the MRHD, based on area under the concentration-time curve (AUC).

8.2 Lactation

Risk Summary

There are no data on the presence of crovalimab-akkz in either human or animal milk, the effects on the breastfed child or on milk production. Endogenous IgG and monoclonal antibodies are transferred in human milk. The effects of local gastrointestinal exposure and limited systemic exposure in the breastfed child to crovalimab-akkz is unknown. Because of the potential for serious adverse reactions in a breastfed child, advise patients that breastfeeding is not recommended during treatment with PIASKY and for 9 months after the final dose.

8.4 Pediatric Use

The safety and effectiveness of PIASKY for the treatment of PNH have been established in pediatric patients 13 years and older with a body weight ≥ 40 kg. Use of PIASKY for this indication in pediatric patients is supported by evidence from adequate and well-controlled studies in adults along with additional pharmacokinetic, pharmacodynamic, efficacy and safety data in pediatric patients aged 13 to 17 years [see Adverse Reactions (6.1), Clinical Pharmacology (12.3), and Clinical Studies (14.1)].

The safety and effectiveness of PIASKY have not been established in pediatric patients less than 13 years of age and in those with body weight < 40 kg.

8.5 Geriatric Use

Clinical studies of PIASKY did not include sufficient numbers of subjects aged 65 and over to determine whether they respond differently from younger subjects. In general, dose selection for elderly patients should be cautious, reflecting the greater frequency of decreased hepatic, renal, or cardiac function and of concomitant disease or other therapy.

Of the 393 PIASKY-treated patients in COMMODORE 1, 2 and 3, 43 (10.9%) were 65 years of age and older. In patients who were complement inhibitor naïve, serious adverse reactions were reported in 1 patient (8%) who was 65 years or older compared to 6 (4%) patients who were 18 to 64 years of age. In patients who previously received a different C5 inhibitor and switched to PIASKY, serious adverse reactions were reported in 3 (7%) patients who were 65 years or older compared to 12 (4%) patients who were 18 to 64 years of age.

11 DESCRIPTION

Crovalimab-akkz, a complement C5 inhibitor, is a humanized monoclonal antibody based on a human IgG1 framework. The recombinant antibody is produced in Chinese hamster ovary CHO cells and consists of two heavy chains (451 amino acid residues each) and two light chains (217 amino acid residues each). The approximate molecular weight is 145 kDa.

PIASKY (crovalimab-akkz) injection is a preservative-free, sterile, clear to opalescent, almost colorless to brownish-yellow, solution supplied in a single-dose vial for intravenous use or subcutaneous use. Intravenous use requires dilution prior to administration.

Each single-dose vial contains a 2 mL solution of crovalimab-akkz (340 mg), arginine hydrochloride (42.2 mg), histidine (9.4 mg), poloxamer 188 (1 mg), and Water for Injection USP. The pH is 5.8. Aspartic acid may be added to adjust the pH.

12 CLINICAL PHARMACOLOGY

12.1 Mechanism of Action

Crovalimab-akkz is a monoclonal antibody that specifically binds with high affinity to the complement protein C5, inhibiting its cleavage into C5a and C5b, preventing the formation of the membrane attack complex (MAC). Crovalimab-akkz inhibits terminal complement-mediated intravascular hemolysis in patients with PNH.

12.2 Pharmacodynamics

Concentration-dependent inhibition of terminal complement activity following treatment with PIASKY was observed in patients with PNH naïve to complement inhibitor therapy and patients switching from another complement C5 inhibitor therapy. Terminal complement activity (CH50 as measured by Liposome Immunoassay [LIA]) inhibition was achieved by the end of the initial PIASKY infusion and was sustained through the duration of PIASKY treatment. Similarly, mean free C5 concentrations declined to low levels (<0.0001 g/L) in comparison to baseline and remained low throughout the treatment period.

12.3 Pharmacokinetics

Crovalimab-akkz exhibits dose proportional pharmacokinetics over the dose range from 75 to 1500 mg when given as a single intravenous infusion and from 100 to 1020 mg when given as a subcutaneous injection. Following the first intravenous loading dose, crovalimab-akkz concentrations exceeded the target threshold for complete terminal complement inhibition (100 µg/mL). After approximately 12 weeks, with the administration of subsequent subcutaneous doses, crovalimab-akkz attained a steady-state plateau of exposure. Pharmacokinetic exposures in patients with PNH are summarized for the recommended dosage of crovalimab-akkz in Table 6.

Table 6 Mean (%CV) Pharmacokinetic Parameters of Crovalimab-akkz in Subjects with Paroxysmal Nocturnal Hemoglobinuria.
Body weight of patients | Ctrough,ss (µg/mL) | Cmax,ss (µg/mL) | AUCτ,ss (µg × day/mL)
≥ 40 kg to < 100 kg | 230 (31.6%) | 292 (30.1%) | 7478 (30.5%)
≥ 100 kg | 205 (31.5%) | 265 (30.9%) | 6748 (30.7%)
AUCτ,ss = area under the concentration-time curve for a dosing interval at steady state; Cmax,ss = maximum concentration during a dosing interval at steady state; Ctrough,ss = trough concentration at steady state.

Absorption

The mean absorption rate constant is 0.126 day^-1 [90% CI: 0.105, 0.176]. Following subcutaneous administration, the bioavailability is 83.0% [90% CI: 69.6, 92.0].

Distribution

The mean central and peripheral volume of distribution is 3.23 L [90% CI: 3.16, 3.29] and 2.32 L [90% CI: 2.02, 2.67], respectively.

Elimination

In PNH treatment-naïve patients, the mean clearance is 0.0791 L/day [90% CI: 0.0678, 0.0872]. The mean estimated terminal half-life is 53.1 days [90% CI: 47.7, 58.6].

Metabolism

Crovalimab-akkz is expected to be catabolized by lysosomal proteolysis into small peptides and amino acids.

Excretion

Crovalimab-akkz is not eliminated via renal or hepatic pathways.

Special Populations

After inclusion of body weight, population pharmacokinetic analyses in patients with PNH showed that age (13-85 years of age), gender, and race (Caucasian, Black, and Asian) did not meaningfully influence the pharmacokinetics of PIASKY. No clinically significant differences in the pharmacokinetics of PIASKY were observed based on renal impairment (mild, moderate, and severe) and mild hepatic impairment. PIASKY has not been studied in patients with moderate or severe hepatic impairment.

Pediatric Patients

Data obtained in PNH clinical studies indicates that exposure in pediatric patients weighing ≥ 40 kg was consistent with that of adult patients.

Patients Switching from Another C5 Inhibitor

In patients switching from another C5 inhibitor (e.g., eculizumab or ravulizumab), a transient increase in clearance is observed due to the formation of transient immune complexes, leading to a faster elimination of PIASKY. However, this transiently different clearance does not require dose adjustment in patients switching from another C5 inhibitor.

12.6 Immunogenicity

The observed incidence of anti-drug antibodies is highly dependent on the sensitivity and specificity of the assay. Differences in assay methods preclude meaningful comparisons of the incidence of anti-drug antibodies in the studies described below with the incidence of anti-drug antibodies in other studies, including other crovalimab-akkz products.

In the active-controlled COMMODORE 2 study, 30% (42/140) of treatment-naïve patients who received PIASKY and 34% (23/67) of patients who switched from treatment with another C5 inhibitor to PIASKY (switch patients) tested positive for anti-crovalimab-akkz-antibodies. The positive antidrug antibodies (ADAs) were detected after a median treatment duration of 48 weeks (range: 0.1 to 108 weeks) in treatment-naïve patients and 24 weeks (range: 0.3 to 76 weeks), in switch patients.

Across COMMODORE 1, COMMODORE 2, and COMMODORE 3, the incidence of treatment-emergent ADAs was 31% (60/191) following a median treatment duration of 52 weeks (range 0.1 to 108 weeks) in treatment-naïve patients and 23% (43/184) following a median treatment duration of 32 weeks (0.3 to 108 weeks) in switch patients.

Among the patients who were randomized to PIASKY, those who developed anti-crovalimab-akkz antibodies had reduced crovalimab-akkz concentrations, geometric mean decrease in the range of 39% to 56%, compared to those who did not develop anti-crovalimab-akkz antibodies through the course of the treatment period in COMMODORE 2. Despite this effect, crovalimab-akkz concentrations remained above 100 µg/mL (the threshold for complete terminal complement inhibition) in more than 80% of ADA-positive patients. Approximately 3% (11/375) of ADA-positive patients had a loss of pharmacological activity (based on CH50 or free C5) coinciding with a loss of exposure and with loss of efficacy, manifesting as a sustained loss of hemolysis control in 1.6% (6/375) of patients with PNH. There was no evidence for a clinical impact of ADA status on the safety profile of PIASKY.

13 NONCLINICAL TOXICOLOGY

13.1 Carcinogenesis, Mutagenesis, Impairment of Fertility

Long-term carcinogenicity studies and genotoxicity studies have not been conducted with crovalimab-akkz. No effects on female or male reproductive organs were observed in cynomolgus monkeys following repeated administration of crovalimab-akkz for up to 6 months with subcutaneous doses up to 100 mg/kg/week which corresponds to 18- and 16- times for males and females, respectively, the MRHD based on AUC.

14. CLINICAL STUDIES

14.1 Paroxysmal Nocturnal Hemoglobinuria

The efficacy of PIASKY in patients with PNH was evaluated in COMMODORE 2 (NCT04434092), an active-controlled, open-label, non-inferiority study that randomized 204 patients (body weight ≥ 40 kg) with PNH not previously treated with a complement inhibitor in a 2:1 ratio to receive either PIASKY (n=135) or eculizumab (n=69). The study additionally enrolled 6 pediatric patients (aged >12 years and body weight ≥ 40 kg) to receive PIASKY in a separate non-randomized cohort.

Patients were required to be vaccinated against Neisseria meningitidis, either within 3 years prior to the start of treatment or within 7 days after starting treatment with PIASKY. Patients vaccinated within 2 weeks prior to initiating PIASKY or after the start of study treatment received prophylactic antibiotics until at least 2 weeks after the vaccination.

A single intravenous loading dose of PIASKY was given on Day 1 (1,000 mg for patients weighing ≥40 kg to <100 kg, or 1,500 mg for patients weighing >100 kg), followed by four additional weekly subcutaneous loading doses of 340 mg on Days 2, 8, 15 and 22. Starting at Day 29, maintenance subcutaneous doses were given every 4 weeks (680 mg for patients weighing ≥40 kg to <100 kg, or 1,020 mg for patients weighing ≥100 kg).

The study consisted of a primary treatment period of 24 weeks, after which patients had the option to continue or switch to PIASKY in an extension period.

Eligible patients had LDH level ≥ 2 × upper limit of normal (ULN) and at least one or more PNH-related signs or symptoms in the past 3 months. Randomization was stratified by the most recent LDH value (≥ 2 to ≤ 4 × ULN, or > 4× ULN) and by the transfusion history (0, > 0 to ≤ 6, or > 6 packed red blood cell (pRBC) units administered within 6 months prior to randomization). In the PIASKY and eculizumab arms, the median PNH clone size was 90.9% and 95.1% for monocytes, 91.4% and 93.6% for granulocytes and 25.3% and 44.6% for erythrocytes, respectively.

Demographics and baseline characteristics of the randomized study population were generally balanced between the treatment arms and are presented in Table 7.

Table 7 Demographics and Baseline Characteristics for COMMODORE 2 (Randomized Population)
Parameters | PIASKY (N= 135) | Eculizumab (N= 69)
Age (years) at PNH diagnosis
Mean (SD) | 35.8 (15.5) | 37.4 (16.4)
Median (range) | 31.0 (11.5- 74.7) | 32.1 (11.2- 76.8)
Age (years) at first administration of the study drug
Mean (SD) | 40.5 (15.2) | 41.9 (16.0)
Median (range) | 36.0 (18-76) | 38.0 (17-78)
<18 years, n (%) | 0 | 2 (2.9%)
18 – 64 years, n (%) | 122 (90.4%) | 58 (84.1%)
≥65 years, n (%) | 13 (9.6%) | 9 (13.0%)
Weight
40 to <100 kg, n (%) | 131 (97.0%) | 66 (95.7%)
≥100 kg, n (%) | 4 (3.0%) | 3 (4.3%)
Sex
Male, n (%) | 77 (57.0%) | 35 (50.7%)
Female, n (%) | 58 (43.0%) | 34 (49.3%)
Race
Asian | 86 (63.7%) | 51 (73.9%)
White | 45 (33.3%) | 16 (23.2%)
Black or African American | 3 (2.2%) | 1 (1.4%)
Unknown | 1 (0.7%) | 1 (1.4%)
Ethnicity
Hispanic or Latino | 18 (13.3%) | 6 (8.7%)
Not Hispanic or Latino | 114 (84.4%) | 61 (88.4%)
Not reported | 3 (2.2%) | 2 (2.9%)
Baseline hemoglobin (g/dL)
Median (range) | 8.5 (6.3-13.5) | 8.5 (5.8-12.9)
LDH levels at baseline (× ULN)
Median (range) | 7.0 (2.0 – 16.3) | 7.7 (2.0 – 20.3)
History of pRBC transfusion in the 12 months prior to screening
Yes, n (%) | 103 (77.4%) | 50 (73.5%)
Number of pRBC units transfused in the 12 months prior to screening
Median (range) | 3.8 (0-43.5) | 3.0 (0-41.0)
History of aplastic anemia
Yes, n (%) | 53 (39.3%) | 26 (37.7%)
History of myelodysplastic syndrome
Yes, n (%) | 6 (4.4%) | 6 (8.7%)
History of Major Adverse Vascular Event
Yes, n (%) | 21 (15.6%) | 10 (14.5%)
Medications at baseline [Includes medications that were started prior to initiation of study treatment and were either stopped before or were ongoing at time of initiation of study treatment.]
Anticoagulants, n (%) | 35 (25.9%) | 17 (24.6%)
Systemic corticosteroids, n (%) | 46 (34.1%) | 25 (36.2%)
Immunosuppressive therapy, n (%) | 23 (17%) | 13 (18.8%)
pRBCs = packed red blood cells

Efficacy was based on hemolysis control, as measured by the mean proportion of patients with LDH ≤ 1.5× ULN from Week 5 to Week 25; and the proportion of patients who achieved transfusion avoidance, defined as patients who were pRBC transfusion-free, from baseline through Week 25. Other efficacy endpoints included the proportion of patients with breakthrough hemolysis and the proportion of patients with stabilized hemoglobin. Breakthrough hemolysis was defined as at least one new or worsening symptom or sign of intravascular hemolysis in the presence of elevated LDH ≥ 2 × ULN after prior reduction of LDH to ≤ 1.5 × ULN on treatment. Hemoglobin stabilization was defined as avoidance of a ≥ 2 g/dL decrease in hemoglobin level from baseline, in the absence of transfusion.

Efficacy results for these endpoints are shown in Table 8.

Table 8 Efficacy Results from COMMODORE 2 (Primary Analysis Population)
 | PIASKY (N=134) [One patient randomized to PIASKY did not have post-baseline LDH and was not included in the primary efficacy analysis] | Eculizumab (N = 69)
Proportion of patients with Transfusion Avoidance, % (95% CI) | 65.7 (56.9, 73.5) | 68.1 (55.7, 78.5)
Difference in proportions [Difference calculated as PIASKY minus eculizumab] , % (95% CI) [Non-inferiority was demonstrated based on the margin pre-specified in the study protocol] | -2.8% (-15.7, 11.1)
Mean proportion of patients achieving hemolysis control, % (95% CI) | 79.3 (72.9, 84.5) | 79.0 (69.7, 86.0)
Odds Ratio [Odds ratio calculated as odds for PIASKY divided by odds for eculizumab] (95% CI) | 1.02 (0.57, 1.82)
Proportion of patients with Breakthrough Hemolysis, % (95% CI) | 10.4 (6.0, 17.2) | 14.5 (7.5, 25.5)
Difference in proportions, % (95% CI) | - 3.9% (-14.8, 5.3)
Proportion of patients with stabilized hemoglobin, % (95% CI) | 63.4 (54.6, 71.5) | 60.9 (48.4, 72.2)
Difference in proportions, % (95% CI) | 2.2 (-11.4, 16.3)
CI = confidence interval

Pediatric Population with PNH Treated with PIASKY

Efficacy was evaluated in 12 pediatric patients (with body weight ≥ 40 kg) treated with PIASKY in COMMODORE 2 (n=7; 13–17 years old), COMMODORE 1 (n=2, 13 – 16 years old) and in a single arm study in patients who were complement-inhibitor naïve, COMMODORE 3 (NCT04654468; n=3; 15–17 years old).

Nine pediatric patients were treatment-naïve, two patients switched from standard dose eculizumab and one patient switched from ravulizumab. Six pediatric patients were females and six were males. Nine patients were Asian, two were White and for one pediatric patient the race was unknown. The proportion of patients with a history of transfusions in the prior 12 months was 58%, with a median number of 1.3 pRBC units (range: 0-40.5) transfused, and a baseline median LDH of 6.4 × ULN (range 1.1-26.6). Aplastic anemia was reported in 50% of patients. All pediatric patients received the same dosing as adult patients based on body weight [see Dosage and Administration (2.2)]. Hemolysis control (defined as LDH ≤1.5 × ULN) from baseline to Week 25 was achieved in 7 of the 9 patients who were treatment-naïve, and the 3 patients switching from eculizumab or ravulizumab to PIASKY maintained hemolysis control through 24 weeks of PIASKY treatment. Nine (six patients who were treatment-naïve and three patients who switched from eculizumab or ravulizumab) out of the 12 pediatric patients achieved transfusion avoidance and hemoglobin stabilization, and no patients had a breakthrough hemolysis event during the 24-week treatment period.

Overall, the treatment effect of PIASKY in pediatric patients with PNH was consistent with that observed in adults with PNH.

16 HOW SUPPLIED/STORAGE AND HANDLING

16.1 How Supplied

PIASKY (crovalimab-akkz) injection is a sterile, preservative-free, clear to opalescent, and almost colorless to brownish-yellow solution. Each PIASKY carton contains one 340 mg/2 mL (170 mg/mL) single-dose vial (NDC 50242-115-01).

16.2 Storage and Handling

- Store refrigerated at 2°C to 8°C (36°F to 46°F) in the outer carton to protect from light. Do not freeze. Do not shake.
- Once removed from the refrigerator, the unopened vial can be kept at room temperature up to 30°C (86°F) in its outer carton for no longer than 7 days.
- Prior to administration, unopened vials of PIASKY may be stored out of the refrigerator at room temperature if needed and then returned to refrigeration. The total combined time out of refrigeration should not exceed 7 days and the temperature should not exceed 30°C (86°F). Discard if stored out of the refrigerator at room temperature for longer than 7 days.

17 PATIENT COUNSELING INFORMATION

Advise the patient to read the FDA-approved patient labeling (Medication Guide).

Serious Meningococcal Infection

Advise patients of the risk of serious meningococcal infection. Inform patients of the need to complete or update their meningococcal vaccinations at least 2 weeks prior to receiving the first dose of PIASKY or receive antibacterial drug prophylaxis if PIASKY treatment must be initiated immediately and they have not previously been vaccinated. Inform patients of the requirement to be revaccinated according to current ACIP recommendations for meningococcal infection while on PIASKY therapy.

Inform patients that vaccination may not prevent serious meningococcal infection and to seek immediate medical attention if the following signs or symptoms occur [see Warnings and Precautions (5.1)].

- fever
- fever and a rash
- headache with nausea or vomiting
- fever with a high heart rate
- headache and a fever
- headache with a stiff neck or stiff back
- confusion
- muscle aches, with flu-like symptoms
- eye sensitive to light

Inform patients that they will be given a Patient Safety Card for PIASKY that they should carry with them at all times during and for 11 months following treatment with PIASKY. This card describes symptoms which, if experienced, should prompt the patient to immediately seek medical evaluation.

PIASKY REMS

PIASKY is available only through a restricted program called PIASKY REMS [see Warnings and Precautions (5.2)].

Inform the patient of the following requirements:

- Patients must receive counseling about the risk of serious meningococcal infections.
- Patients must receive written educational materials about this risk.
- Patients must be instructed to carry the Patient Safety Card with them at all times during and for 11 months following treatment with PIASKY.
- Patients must be instructed to complete or update meningococcal vaccines for serogroups A, C, W, Y and B per ACIP recommendations as directed by the prescriber prior to treatment with PIASKY.
- Patients must receive antibiotics as directed by the prescriber if they are not up to date with meningococcal vaccines and have to start PIASKY right away.

Type III Hypersensitivity Reactions

Inform patients of the risk of experiencing a Type III hypersensitivity reaction in the first 30 days after switching from another C5 inhibitor to PIASKY (or if they are planning to switch from PIASKY to another C5 inhibitor) [see Warnings and Precautions (5.3)]. Inform patients about the signs and symptoms of a Type III hypersensitivity reaction, and advise patients to seek immediate medical attention if the following signs or symptoms occur:

- rash
- itching
- joint pain
- numbness and tingling or a feeling of pins and needles, especially of the hands and feet

Other Infections

Counsel patients of the increased risk of infections, particularly those due to encapsulated bacteria, especially Neisseria species [see Warnings and Precautions (5.4)]. Advise patients of the need for vaccination against Streptococcus pneumoniae infections according to current ACIP recommendations. Inform parents or caregivers of children receiving PIASKY that their child should be vaccinated against Streptococcus pneumoniae and Haemophilus influenzae type b (Hib) according to current medical guidelines.

Advise patients to report any new signs and symptoms of infection.

Infusion- and Injection-Related Reactions

Advise patients that administration of PIASKY may result in infusion-related reactions or systemic injection-related reactions depending on the route of administration [see Warnings and Precautions (5.5)]. Advise patients to seek immediate medical attention if symptoms of serious allergic reactions occur.

Discontinuation of PIASKY

Inform patients that they may develop hemolysis due to PNH when PIASKY is discontinued and that they will be closely monitored by their healthcare professional for at least 20 weeks following PIASKY discontinuation [see Warnings and Precautions (5.6)]. Inform patients who discontinue PIASKY to keep the Patient Safety Card with them for 11 months after the last PIASKY dose, because the increased risk of meningococcal infection persists for several months following discontinuation of PIASKY [see Warnings and Precautions (5.1 and 5.2)].

Lactation

Advise patients it is not recommended to breastfeed during treatment with PIASKY and for 9 months after the final dose [see Use in Specific Populations (8.2)].

Manufactured by:
Genentech, Inc.
A Member of the Roche Group
1 DNA Way
South San Francisco, CA 94080-4990
U.S. License No.: 1048

PIASKY is a registered trademark
of Chugai Pharmaceutical Co., Ltd., Tokyo, Japan.
©2024 Genentech, Inc.

MEDICATION GUIDE
PIASKY (pea-UH-sky)
(crovalimab-akkz)
injection, for intravenous or subcutaneous use

What is the most important information I should know about PIASKY?

PIASKY is a medicine that affects your immune system. PIASKY may lower the ability of your immune system to fight infections.

- PIASKY increases your chance of getting serious infections caused by Neisseria meningitidis. Meningococcal infections may quickly become life-threatening or cause death if not recognized and treated early.
  - You must complete or update your meningococcal vaccines at least 2 weeks before your first dose of PIASKY.
  - If you have not completed your meningococcal vaccines and PIASKY must be started right away, you should receive the required vaccines as soon as possible.
  - If you have not been vaccinated and PIASKY must be started right away, you should also receive antibiotics to take for as long as your healthcare provider tells you to.
  - If you had a meningococcal vaccine in the past, you might need additional vaccines before starting PIASKY. Your healthcare provider will decide if you need additional meningococcal vaccines.
  - Meningococcal vaccines do not prevent all meningococcal infections. Call your healthcare provider or get emergency medical care right away if you get any of these signs and symptoms of a serious meningococcal infection:

- fever
- fever and a rash
- fever with a high heart rate
- fever with a headache
- headache with nausea or vomiting

- headache with a stiff neck or stiff back
- confusion
- muscle aches, with flu-like symptoms
- eyes sensitive to light

Your healthcare provider will give you a Patient Safety Card about the risk of serious meningococcal infection.
Carry it with you at all times during treatment and for 11 months after your last dose of PIASKY. Your risk of meningococcal infection may continue for several months after your last dose of PIASKY. It is important to show this card to any healthcare provider who treats you. This will help them diagnose and treat you quickly.
PIASKY is only available through a program called the PIASKY Risk Evaluation and Mitigation Strategy (PIASKY REMS). Before you can receive PIASKY, your healthcare provider must:

- enroll in the PIASKY REMS program
- counsel you about the risk of serious meningococcal infection
- give you information about the signs and symptoms of serious meningococcal infection
- make sure that you are vaccinated against serious infections caused by meningococcal bacteria and that you receive antibiotics if you need to start PIASKY right away and you are not up to date on your vaccines
- give you a Patient Safety Card about your risk of meningococcal infection, as discussed above

- Immune system reactions called Type III hypersensitivity reactions are common during treatment with PIASKY and can also be serious. If you are currently being treated with or have been treated with another C5 inhibitor medicine and you switch to PIASKY, PIASKY may cause Type III hypersensitivity reactions. People may also develop Type III hypersensitivity reactions when they switch from PIASKY to another C5 inhibitor medicine. If you have been treated with another C5 inhibitor medicine and you switch to PIASKY, or if you have been treated with PIASKY and you switch to another C5 inhibitor medicine, your healthcare provider should monitor you for 30 days after you switch medicines. Call your healthcare provider or go to the nearest emergency room right away if you develop any signs and symptoms of Type III hypersensitivity reactions, including:

- joint pain
- muscle or bone pain
- rash or skin problems
- itching
- headache
- kidney problems

- numbness and tingling or a feeling of pins and needles, especially of the hands and feet
- fever
- weakness, tiredness, or lack of energy
- stomach trouble or pain

- PIASKY may also increase the risk of other types of serious infections caused by encapsulated bacteria, including infections caused by Neisseria spp., Streptococcus pneumoniae, and Haemophilus influenzae and Neisseria gonorrhoeae.
  - If you receive treatment with PIASKY, you should receive vaccines against Streptococcus pneumoniae.
  - If your child receives treatment with PIASKY, your child should receive vaccines against Streptococcus pneumoniae and may receive vaccines against Haemophilus influenzae, depending on their age.
  Call your healthcare provider right away if you have any new signs or symptoms of infection such as:

- fever of 100.4°F (38°C) or higher
- cough
- chest pain
- tiredness
- feeling short of breath

- painful rash
- sore throat
- burning pain when passing urine
- feeling weak or generally unwell

For more information about side effects, see "What are the possible side effects of PIASKY?"

What is PIASKY?
PIASKY is a prescription medicine used to treat a disease called paroxysmal nocturnal hemoglobinuria (PNH) in adults and children 13 years of age and older who weigh at least 88 pounds (40 kg).
It is not known if PIASKY is safe and effective in children under 13 years of age and in people who weigh less than 88 pounds (40 kg).

Who should not receive PIASKY?
Do not receive PIASKY if you:

- have a serious meningococcal infection caused by Neisseria meningitidis when you are starting PIASKY treatment.
- are allergic to crovalimab or any of the ingredients in PIASKY. See the end of this Medication Guide for a complete list of ingredients in PIASKY.

Before receiving PIASKY tell your healthcare provider about all of your medical conditions, including if you:

- have an infection or fever.
- are pregnant or plan to become pregnant. It is not known if PIASKY will harm your unborn baby.
- are breastfeeding or plan to breastfeed. It is not known if PIASKY passes into your breast milk. You should not breastfeed during treatment with PIASKY and for 9 months after your final dose.

Tell your healthcare provider about all the medicines you take, including prescription and over-the-counter medicines, vitamins, and herbal supplements. PIASKY and other medicines can affect each other, causing side effects.
Especially tell your healthcare provider if you are currently being treated with or have ever been treated with any other complement C5 inhibitor (C5 inhibitor) medicine. PIASKY is a C5 inhibitor medicine. Ask your healthcare provider if you are not sure if you have been treated with a C5 inhibitor medicine. See "What are the possible side effects of PIASKY?"
Know the medicines you take and the vaccines you receive. Keep a list of them to show your healthcare provider and pharmacist when you get a new medicine.

How should I receive PIASKY?

- Your healthcare provider will give you your PIASKY treatment.
- Your first dose will be given through a vein by intravenous (IV) infusion over 60 to 90 minutes on Day 1 by your healthcare provider. This is the first loading dose.
- Another loading dose will be given as an injection under the skin (subcutaneous) on Days 2, 8, 15, and 22.
- Your maintenance doses will begin on Day 29 and then will be given every 4 weeks as a subcutaneous injection.
- Your healthcare provider will prescribe the dose based on your weight. If your weight changes, tell your healthcare provider.
- Talk to your healthcare provider if you miss receiving an entire dose or part of your dose of PIASKY.
- If you are changing treatment from another C5 inhibitor such as eculizumab or ravulizumab to PIASKY, you should receive your first loading dose of PIASKY no sooner than the time you would have received your next scheduled dose of eculizumab or ravulizumab.
- If you stop taking PIASKY and do not switch to another treatment for your PNH, your healthcare provider will need to monitor you closely for at least 20 weeks after stopping PIASKY. Stopping treatment with PIASKY may cause a breakdown of red blood cells due to PNH.
  Symptoms or problems that can happen due to red blood cell breakdown include:

- a lower number of red blood cells (anemia)
- blood in your urine or dark urine
- feeling short of breath
- feeling tired or low energy (fatigue)

- stomach pain
- blood clotting (thrombosis)
- difficulty swallowing
- difficulty getting or keeping an erection (erectile dysfunction)
- kidneys not working properly

What are the possible side effects of PIASKY?

PIASKY may cause serious side effects including:

- See "What is the most important information I should know about PIASKY?"
- Infusion- and injection-related reactions. Infusion- or injection-related reactions may happen during or after your PIASKY infusion or injection. Symptoms may include headache, pain at the infusion or injection site or pain in other parts of your body, swelling, bruising or bleeding, red skin, itching and rash. PIASKY can also cause serious allergic reactions. If you have an infusion-related reaction, your healthcare provider may need to infuse PIASKY more slowly, temporarily stop your infusion, or completely stop PIASKY if you develop a serious allergic reaction. Call your healthcare provider right away or go to the nearest emergency room if you develop any signs or symptoms of a serious allergic reaction, including:

- shortness of breath or trouble breathing
- pain or tightness in your chest
- wheezing
- feeling dizzy or lightheaded

- swelling of the throat, lips, tongue, or face
- skin itching, hives, or rash
- fever or chills

The most common side effects of PIASKY include:

- infusion-related reactions
- respiratory tract infections including infections of the lungs, cold symptoms, and pain or swelling of the nose or throat

- viral infections
- Type III hypersensitivity reactions

Tell your healthcare provider about any side effect that bothers you or that does not go away.
These are not all of the possible side effects of PIASKY. Call your doctor for medical advice about side effects. You may report side effects to FDA at 1-800-FDA-1088.

General information about the safe and effective use of PIASKY.
Medicines are sometimes prescribed for purposes other than those listed in a Medication Guide. Do not use PIASKY for a condition for which it was not prescribed. You can ask your pharmacist or healthcare provider for information about PIASKY that is written for health professionals.

What are the ingredients in PIASKY?
Active ingredient: crovalimab-akkz
Inactive ingredients: arginine hydrochloride, histidine, poloxamer 188, and Water for Injection. Aspartic acid may be added to adjust the pH.
Manufactured by: Genentech, Inc., A Member of the Roche Group, 1 DNA Way, South San Francisco, CA 94080-4990
U.S. License No.: 1048
PIASKY is a registered trademark of Chugai Pharmaceutical Co., Ltd., Tokyo, Japan
©2024 Genentech, Inc. All rights reserved. For more information, go to www.PIASKY.com or call 1-877-436-3683.

This Medication Guide has been approved by the U.S. Food and Drug Administration

Issued: 06/2024

PRINCIPAL DISPLAY PANEL - 340 mg/2 mL Vial Carton

NDC 50242-115-01

Piasky®
(crovalimab-akkz)
Injection

340 mg/2 mL
(170 mg/mL)

For Intravenous Infusion After Dilution
or Subcutaneous Use.

Single-Dose Vial.

Administered by Healthcare Professionals Only.

Discard unused portion.

ATTENTION: Dispense the enclosed
Medication Guide to each patient.

1 vial

Rx only

Genentech

11005534